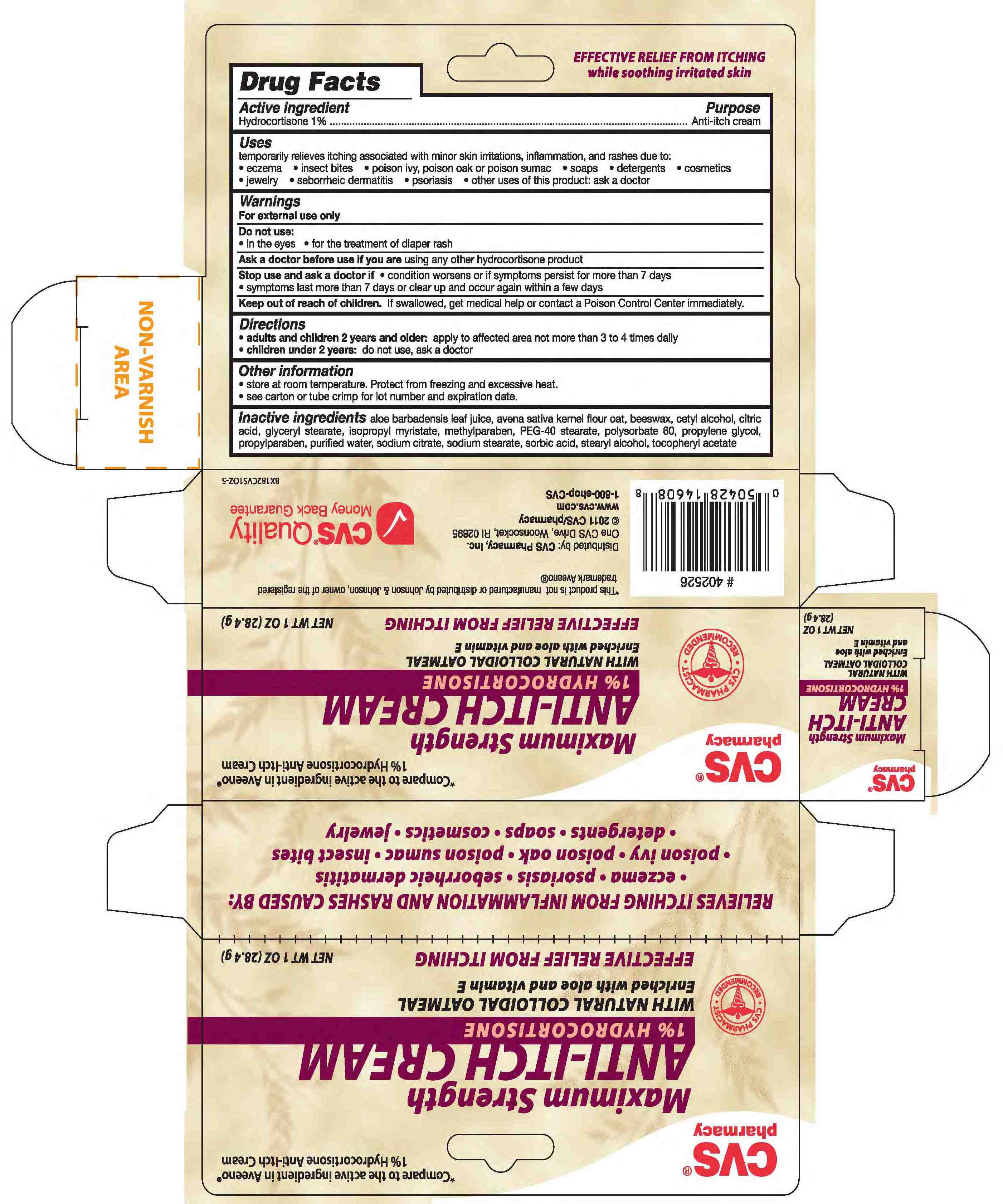 DRUG LABEL: HYDROCORTISONE
NDC: 59779-322 | Form: CREAM
Manufacturer: CVS Pharmacy
Category: otc | Type: HUMAN OTC DRUG LABEL
Date: 20110216

ACTIVE INGREDIENTS: HYDROCORTISONE 10 mg/1 g
INACTIVE INGREDIENTS: WATER; CETYL ALCOHOL; GLYCERYL MONOSTEARATE; ISOPROPYL MYRISTATE; METHYLPARABEN; POLYOXYL 40 STEARATE; POLYSORBATE 60; PROPYLENE GLYCOL; PROPYLPARABEN; ANHYDROUS TRISODIUM CITRATE; SORBIC ACID; SODIUM STEARATE; STEARYL ALCOHOL; .ALPHA.-TOCOPHEROL ACETATE, D-; WHITE WAX; OATMEAL; ANHYDROUS CITRIC ACID; ALOE VERA LEAF

drug facts

Active ingredient Purpose
Hydrocortisone 1%.................................... Anti-itch cream

Uses
temporarily relieves itching associated with minor skin irritations, inflammation and rashes due to:
- eczema - insect bites - poison ivy, poison oak or poison sumac - soaps - detergents - cosmetics
- jewlery - seborrheic dermatitis - psoriasis - other uses of this product: ask a doctor

Keep out of reach of children. If swallowed, get medical help or contact
a Poison Control Center immediately.

Uses
temporarily relieves itching associated with minor skin irritations, inflammation and rashes due to:
- eczema - insect bites - poison ivy, poison oak or poison sumac - soaps - detergents - cosmetics
- jewlery - seborrheic dermatitis - psoriasis - other uses of this product: ask a doctor
Other information
- store at room temperature. Protect from freezing and excessive heat.
- see carton or tube crimp for lot number and expiration date.

Warnings
For external use only.
Do not use:
- in the eyes - for the treatment of diaper rash
Ask a doctor before use if you are using any other hydrocortisone product
Stop use and ask a doctor if
- condition worsens, or if symptoms persist for more than 7 days
- symptoms last more than 7 days or clear up and occur again within a few days
Keep out of reach of children. If swallowed, get medical help or contact a Poison Control Center immediately.

Directions
- adults and children 2 years and older:apply to affected area not more than 3 to 4 times daily
- children under 2 years:do not use, ask a doctor

Inactive Ingredients
aloe barbadensis leaf juice, avena sativa kernal flour oat, beeswax, cetyl alcohol, citric acid,
glyceryl stearate, isopropyl myristate, methylparaben, PEG-40 stearate, polysorbate 60,
propylene glycol, propylparaben, purified water, sodium citrate, sodium stearate, sorbic acid,
stearyl alcohol, tocopheryl acetate